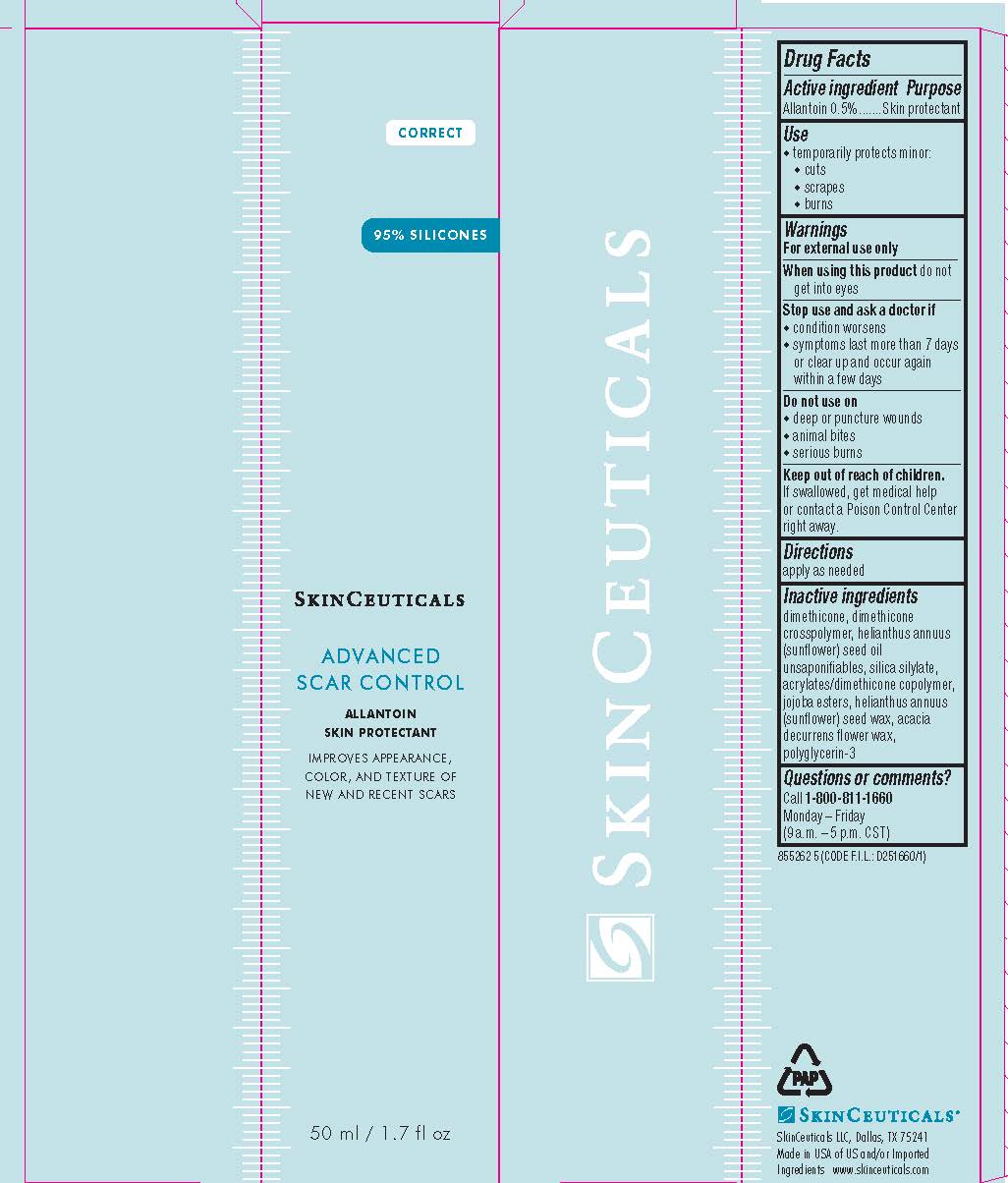 DRUG LABEL: SkinCeuticals Advanced Scar Control Skin Protectant
NDC: 49967-783 | Form: GEL
Manufacturer: L'Oreal USA Products Inc
Category: otc | Type: HUMAN OTC DRUG LABEL
Date: 20241228

ACTIVE INGREDIENTS: ALLANTOIN 5 mg/1 mL
INACTIVE INGREDIENTS: DIMETHICONE; DIMETHICONE CROSSPOLYMER (450000 MPA.S AT 12% IN CYCLOPENTASILOXANE); SUNFLOWER OIL; HYDROGENATED JOJOBA OIL, RANDOMIZED; HELIANTHUS ANNUUS SEED WAX; ACACIA DECURRENS FLOWER WAX; POLYGLYCERIN-3

Drug Facts

Active ingredient

Allantoin 0.5%

Purpose

Skin protectant

Uses

temporarily protects minor:

- cuts
- scrapes
- burns

Warnings

For external use only

Do not use on

- deep or puncture wounds
- animal bites
- serious burns

When using this product

do not get into eyes

Stop use and ask a doctor if

- condition worsens
- symptoms last more than 7 days or clear up and occur again within a few days

Keep out of reach of children.

If swallowed, get medical help or contact a Poison Control Center right away.

Directions

● apply as needed

Inactive ingredients

dimethicone, dimethicone crosspolymer, helianthus annuus (sunflower) seed oil unsaponifiables, silica silylate, acrylates/dimethicone copolymer, jojoba esters, helianthus annuus (sunflower) seed wax, acacia decurrens flower wax, polyglycerin-3

Questions or comments?

Call 1-800-811-1660

Monday - Friday (9 a.m. - 5 p.m. CST)